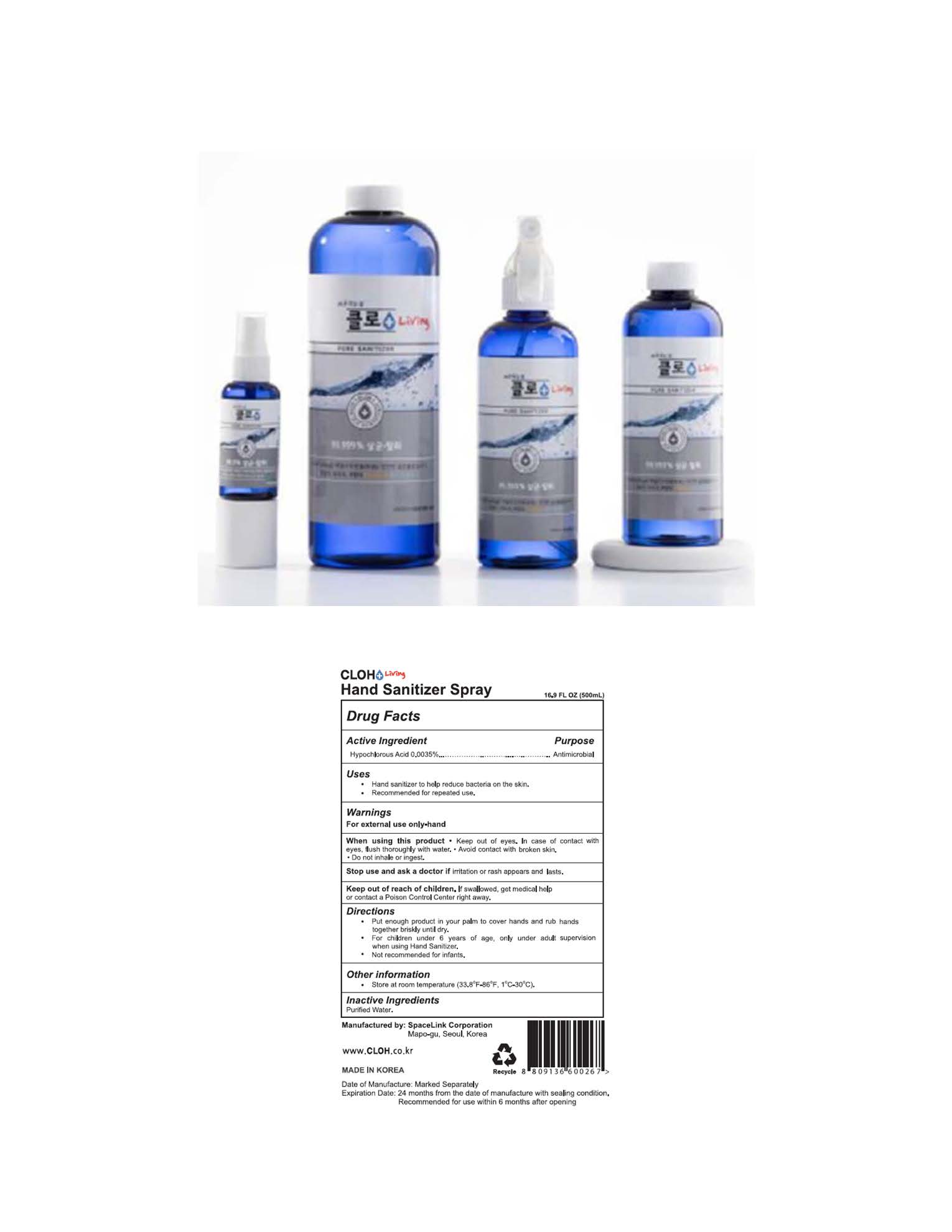 DRUG LABEL: CLOH Living Hand Sanitizer
NDC: 79617-200 | Form: SPRAY
Manufacturer: SpaceLink Corporation
Category: otc | Type: HUMAN OTC DRUG LABEL
Date: 20220617

ACTIVE INGREDIENTS: HYPOCHLOROUS ACID 0.0035 g/100 mL
INACTIVE INGREDIENTS: WATER

Active Ingredient(s)

Hypochlorous Acid 0.0035%. Purpose: Antimicrobial

Purpose

Antimicrobial, Hand Sanitizer

Use

Hand sanitizer to help reduce bacteria on the skin.
Recommended for repeated use.

Warnings

For external use only-hand.

Do not use

- in children less than 2 months of age
- on open skin wounds

When using this product keep out of eyes, ears, and mouth. In case of contact with eyes, rinse eyes thoroughly with water.
Stop use and ask a doctor if irritation or rash occurs. These may be signs of a serious condition.
Keep out of reach of children. If swallowed, get medical help or contact a Poison Control Center right away.

Stop use and ask a doctor if irritation or rash occurs. These may be signs of a serious condition.

Keep out of reach of children. If swallowed, get medical help or contact a Poison Control Center right away.

Directions

- Place enough product on hands to cover all surfaces. Rub hands together until dry.
- For children under 6, use only under adult supervision.
- Not recommended for infants.

Other information

- Store at room temperature 1oC-30oC (33.8oF-86oF).

Inactive ingredients

Purified Water.